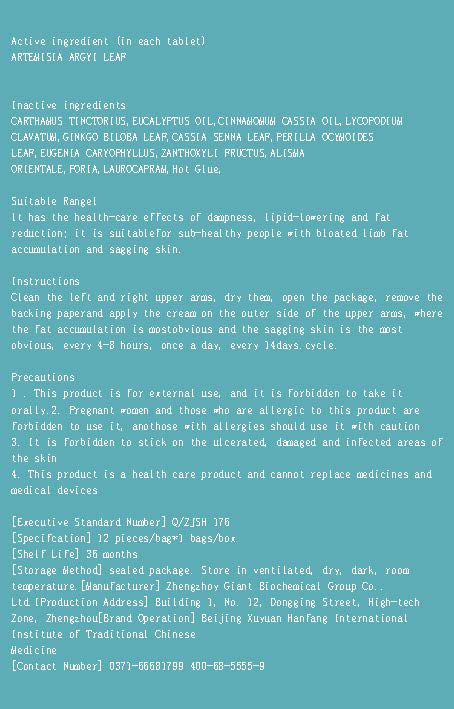 DRUG LABEL: ARTEMISIA ARGYI LEAF
NDC: 52784-010 | Form: PATCH
Manufacturer: ZHENGZHOU GIANT BIOCHEMISTRY GROUP CO.,LTD
Category: homeopathic | Type: HUMAN OTC DRUG LABEL
Date: 20230228

ACTIVE INGREDIENTS: ARTEMISIA ARGYI LEAF 16 g/100 g
INACTIVE INGREDIENTS: EUCALYPTUS OIL; PERILLA FRUTESCENS LEAF; CLOVE; ZANTHOXYLUM BUNGEANUM FRUIT; ALISMA PLANTAGO-AQUATICA SUBSP. ORIENTALE ROOT; LAUROCAPRAM; SAFFLOWER; CHINESE CINNAMON OIL; LYCOPODIUM CLAVATUM WHOLE; GINKGO; SENNA LEAF; FU LING

Arm Slim Sticker

Active ingredient

ARTEMISIA ARGYI LEAF

Suitable Rangel

lt has the health-care effects of dampness，lipid-lowering and fatreduction; it is suitablefor sub-healthy people with bloated limb fataccumulation and sagging skin.

Keep out of reach of children

Instructions

Apply to skin area to relieve symptoms

Warning

1 . This product is for external use, and it is forbidden to take itorally.
2. Pregnant women and those who are allergic to this product areforbidden to use it, anothose with allergies should use it with caution
3. It is forbidden to stick on the ulcerated,damaged and infected areas ofthe skin
4. This product is a health care product and cannot replace medicines andmedical devices

DOSAGE AND ADMINISTRATION

Clean the left and right upper arms，dry them,open the package，remove the backing paperand apply the cream on the outer side of the upper arms,wherethe fat accumulation is mostobvious and the sagging skin is the most obvious，every 4-8 hours，once a day,every 14days.cycle.

STORAGE AND HANDLING

[Shelf Life] 36 months

INACTIVE INGREDIENT

CARTHAMUS TINCTORIUS, EUCALYPTUS OIL, CINNAMOMUM CASSIA OIL, LYCOPODIUM CLAVATUM, GINKGO BILOBA LEAF, CASSIA SENNA LEAF, PERILLA OCYMOIDES LEAF, EUGENIA CARYOPHYLLUS, ZANTHOXYLI FRUCTUS, ALISMA ORIENTALE
PORIA, LAUROCAPRAM, Hot Glue